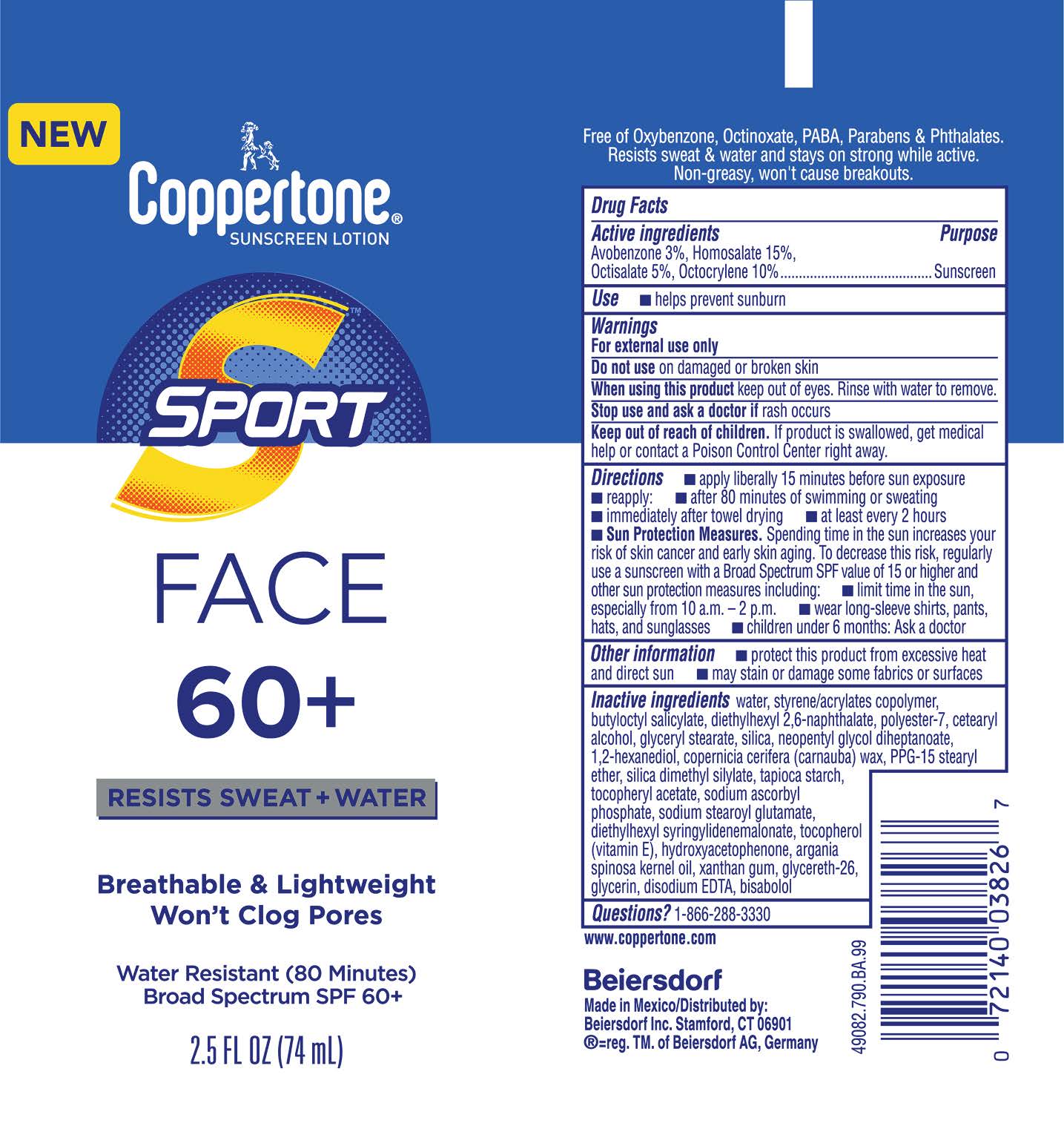 DRUG LABEL: Coppertone Sport Face SPF 60 Plus Sunscreen
NDC: 66800-9013 | Form: LOTION
Manufacturer: Beiersdorf Inc
Category: otc | Type: HUMAN OTC DRUG LABEL
Date: 20251231

ACTIVE INGREDIENTS: OCTOCRYLENE 10 g/100 g; HOMOSALATE 15 g/100 g; AVOBENZONE 3 g/100 g; OCTISALATE 5 g/100 g
INACTIVE INGREDIENTS: CETOSTEARYL ALCOHOL; ARGANIA SPINOSA WHOLE; SODIUM ASCORBYL PHOSPHATE; GLYCERETH-26; DISODIUM EDTA-COPPER; DIETHYLHEXYL 2,6-NAPHTHALATE; PPG-15 STEARYL ETHER; WATER; STYRENE/ACRYLAMIDE COPOLYMER (500000 MW); GLYCERYL STEARATE SE; SILICON DIOXIDE; NEOPENTYL GLYCOL DIHEPTANOATE; 1,2-HEXANEDIOL; SILICA DIMETHYL SILYLATE; POLYESTER-7; HYDROXYACETOPHENONE; XANTHAN GUM; .ALPHA.-TOCOPHEROL ACETATE; .ALPHA.-BISABOLOL, (+/-)-; TOCOPHEROL; BUTYLOCTYL SALICYLATE; STARCH, TAPIOCA; SODIUM STEAROYL GLUTAMATE; DIETHYLHEXYL SYRINGYLIDENEMALONATE; CARNAUBA WAX

Sport Face SPF 60+ Lotion

Active ingredients

Avobenzone 3%, Homosalate 15%, Octisalate 5%, Octocrylene 10%

Purpose

Sunscreen

Use

■ helps prevent sunburn

Warnings

For external use only

Do not useon damaged or broken skin

WHEN USING

When using this productkeep out of eyes. Rinse with water to remove.

Stop use and ask a doctor ifrash occurs

Keep out of reach of children.If product is swallowed, get medical help or contact a Poison Control Center right away.

Directions

■ apply liberally 15 minutes before sun exposure

■ reapply:

■ after 80 minutes of swimming or sweating

■ immediately after towel drying

■ at least every 2 hours

■ Sun Protection Measures.Spending time in the sun increases your risk of skin cancer and early skin aging. To decrease this risk, regularly use a sunscreen with a Broad Spectrum SPF value of 15 or higher and other sun protection measures including:

■ limit time in the sun, especially from 10 a.m. – 2 p.m.

■ wear long-sleeve shirts, pants, hats, and sunglasses

■ children under 6 months: Ask a doctor

Other information

■ protect this product from excessive heat and direct sun

■ may stain or damage some fabrics or surfaces

Inactive ingredients

water, styrene/acrylates copolymer, butyloctyl salicylate, diethylhexyl 2,6-naphthalate, polyester-7, cetearyl alcohol, glyceryl stearate, silica, neopentyl glycol diheptanoate, 1,2-hexanediol, copernicia cerifera (carnauba) wax, PPG-15 stearyl ether, silica dimethyl silylate, tapioca starch, tocopheryl acetate, sodium ascorbyl phosphate, sodium stearoyl glutamate, diethylhexyl syringylidenemalonate, tocopherol (vitamin E), hydroxyacetophenone, argania spinosa kernel oil, xanthan gum, glycereth-26, glycerin, disodium EDTA, bisabolol

Questions?

1-866-3330

PACKAGE LABEL

Coppertone®Sunscreen Lotion

Sport

Face

60+

Resists Sweat + Water

Breathable & Lightweight

Water Resistant (80 Minutes)

Broad Spectrum SPF 60+